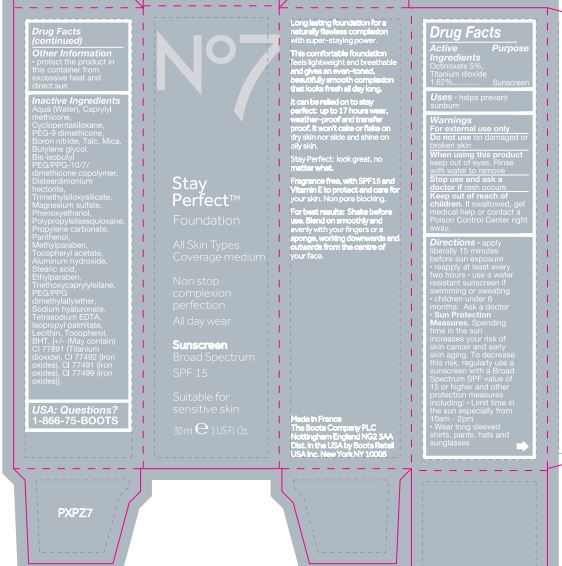 DRUG LABEL: No7 Stay Perfect Foundation Sunscreen Broad Spectrum SPF 15 Deeply Beige
NDC: 61589-1846 | Form: CREAM
Manufacturer: BCM Cosmetique SAS
Category: otc | Type: HUMAN OTC DRUG LABEL
Date: 20191220

ACTIVE INGREDIENTS: Octinoxate 7.5 g/30 g
INACTIVE INGREDIENTS: WATER; CAPRYLYL TRIMETHICONE; PEG-9 DIMETHICONE (400 CST); BORON NITRIDE; TRIMETHYLSILOXYSILICATE (M/Q 0.6-0.8); TALC; MICA; LECITHIN, SOYBEAN; DISTEARDIMONIUM HECTORITE; BUTYLENE GLYCOL; MAGNESIUM SULFATE, UNSPECIFIED; PHENOXYETHANOL; .ALPHA.-TOCOPHEROL ACETATE; METHYLPARABEN; ETHYLPARABEN; TRIETHOXYCAPRYLYLSILANE; HYALURONATE SODIUM; TOCOPHEROL; PANTHENOL; ALUMINUM HYDROXIDE; STEARIC ACID; ISOPROPYL PALMITATE; FERRIC OXIDE YELLOW; TITANIUM DIOXIDE; FERRIC OXIDE RED; FERROSOFERRIC OXIDE

No7 Stay Perfect Foundation Sunscreen Broad Spectrum SPF15 Deeply Beige

Carton Active Ingredients Section

Active Ingredients

Octinoxate 5% Titanium dioxide 1.62%

Uses

Uses - helps prevent sunburn

Warnings

For external use only

Do not use on damaged or broken skin

When using this product keep out of eyes. Rinse with water to remove

Ask a doctor

Stop use and ask a doctor if rash occurs.

Keep out of reach of children. If swallowed, get medical help or contact a Poison Control Center right away.

Directions

Directions for suncreen use

apply liberally 15 minutes before sun exposure

reapply at least every 2 hours

use a water resistant sunscreen if swimming or sweating

children under 6 monhts of age: Ask a doctor

Sun Protection Measures. Spending time in the sun increases your risk of skin cancer and early skin aging. To decrease this risk, regularly use a sunscreen with a Broad Spectrum SPF value of 15 or higher and other sun protection measures including:

limit time in the sun, especially from 10 a.m. - 2 p.m.

wear long-sleeved shirts, pants, hats, and sunglasses

Other information

Protect the product in this container from excessive heat and direct sun

Inactive ingredients

Aqua(Water), Caprylyl methicone, Cyclopentasiloxane, Boron nitride, PEG-9 dimethicone, Talc, Mica, Disteardimonium hectorite, Butylene glycol, Bis-isobutyl PEG/PPG-10-7 dimethicone crosspolymer,Trimethylsiloxysilicate, Magnesium sulfate, Phenoxyethanol, Polypropylsilsesquioxane, Panthenol,Tocopheryl acetate, Methylparaben, Aluminum hydroxide, Ethylparaben, Stearic acid, Triethoxycaprylylsilane, PEG/PPG dimethylallylether, Sodium hyaluronate, Tetrasodium EDTA, Isopropyl palmitate, Lecithin, BHT, Tocopherol, , CI 77492(Iron oxides), CI 77891(Titanium dioxide) CI 77491(Iron oxides)CI 77499(Iron oxides)

Description

Long lasting foundation for a naturally flawless complexion with super-staying power.

This comfortable foundation feels lightweight and breathable and gives an even-toned beautifully smooth complexion that looks fresh all day long.

Stay Perfect: look great, no matter what.

Fragrance free,with SPF 15 and Vitamin E to protect and care for your skin. Non pore blocking.

For Best Results: Shake before use. Blend smoothly and evenly with your fingers or a sponge, working downwards and outwards from the centre of your face.

It can be relied on to stay perfect: up to 17 hours wear, weather-proof and transfer proof. It won't cake or slake on dry skin nor slide and shine on oily skin.

Suitable for sensitive skin.

Information

The Boots Company PLC

Nottingham England NG2 3AA

Dist. by Boots Retail USa Inc.

Norwalk CT 06851 USA

Made in France

www.boots.com

Jar label

No7 Stay Perfect Foundation Sunscreen Broad Spectrum SPF 15

30ml e 1 US Fl.Oz.

Active ingredients: Octinoxate 5.0% Titanium dioxide 1.62%

Warnings

warning: Avoid contact with eyes. If product gets into the eyes, rinse well with water immediately.

Description

Non stop complexion perfection

All day wear

Information

The Boots Company PLC

Nottingham England NG2 3AA.

Dist. by Boots Retail USA Inc.

Norwalk CT 06851 USA

Made in france

www.boots.com

Carton